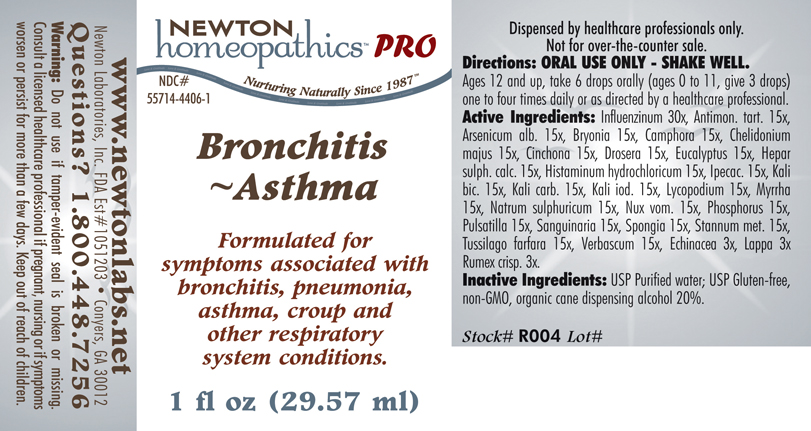 DRUG LABEL: Bronchitis-Asthma 
NDC: 55714-4406 | Form: LIQUID
Manufacturer: Newton Laboratories, Inc.
Category: homeopathic | Type: HUMAN PRESCRIPTION DRUG LABEL
Date: 20110601

ACTIVE INGREDIENTS: Influenza A Virus 30 [hp_X]/1 mL; Antimony Potassium Tartrate 15 [hp_X]/1 mL; Arsenic Trioxide 15 [hp_X]/1 mL; Bryonia Alba Root 15 [hp_X]/1 mL; Camphor (natural) 15 [hp_X]/1 mL; Chelidonium Majus 15 [hp_X]/1 mL; Cinchona Officinalis Bark 15 [hp_X]/1 mL; Drosera Rotundifolia 15 [hp_X]/1 mL; Eucalyptus Globulus Leaf 15 [hp_X]/1 mL; Calcium Sulfide 15 [hp_X]/1 mL; Histamine Dihydrochloride 15 [hp_X]/1 mL; Ipecac 15 [hp_X]/1 mL; Potassium Dichromate 15 [hp_X]/1 mL; Potassium Carbonate 15 [hp_X]/1 mL; Potassium Iodide 15 [hp_X]/1 mL; Lycopodium Clavatum Spore 15 [hp_X]/1 mL; Myrrh 15 [hp_X]/1 mL; Sodium Sulfate 15 [hp_X]/1 mL; Strychnos Nux-vomica Seed 15 [hp_X]/1 mL; Phosphorus 15 [hp_X]/1 mL; Pulsatilla Vulgaris 15 [hp_X]/1 mL; Sanguinaria Canadensis Root 15 [hp_X]/1 mL; Spongia Officinalis Skeleton, Roasted 15 [hp_X]/1 mL; Tin 15 [hp_X]/1 mL; Tussilago Farfara 15 [hp_X]/1 mL; Verbascum Thapsus 15 [hp_X]/1 mL; Echinacea, Unspecified 3 [hp_X]/1 mL; Arctium Lappa Root 3 [hp_X]/1 mL; Rumex Crispus Root 3 [hp_X]/1 mL; Influenza B Virus 30 [hp_X]/1 mL
INACTIVE INGREDIENTS: Alcohol

Bronchitis Asthma

PRODUCT NAME & INDICATIONS SECTION

Bronchitis-Asthma Formulated for symptoms associated with bronchitis, pneumonia, asthma, croup and other respiratory system conditions.

DIRECTION SECTION

Directions: ORAL USE ONLY - SHAKE WELL. Ages 12 and up, take 6 drops orally (ages 0 to 11, give 3 drops) one to four times daily or as directed by a healthcare professional.

ACTIVE INGREDIENT SECTION

Active Ingredients: Influenzinum 30x, Antimon. tart. 15x, Arsenicum alb. 15x, Bryonia 15x, Camphora 15x, Chelidonium majus 15x, Cinchona 15x, Drosera 15x, Eucalyptus 15x, Hepar sulph. calc. 15x, Histaminum hydrochloricum 15x, Ipecac. 15x, Kali bic. 15x, Kali carb. 15x, Kali iod. 15x, Lycopodium 15x, Myrrha 15x, Natrum sulphuricum 15x, Nux vom. 15x, Phosphorus 15x, Pulsatilla 15x, Sanguinaria 15x, Spongia 15x, Stannum met. 15x, Tussilago farfara 15x, Verbascum 15x, Echinacea 3x, Lappa 3x, Rumex crisp. 3x.

INACTIVE INGREDIENT SECTION

Inactive Ingredients: USP Purified water; USP Gluten-free,non-GMO, organic cane dispensing alcohol 20%

PURPOSE SECTION

Formulated for symptoms associated with bronchitis, pneumonia, asthma, croup and other respiratory system conditions.

QUESTIONS? SECTION

www.newtonlabs.net Newton Laboratories, Inc. FDA Est # 1051203 - Conyers, GA 30012
Questions? 1.800.448.7256

WARNINGS SECTION

Warning: Do not use if tamper- evident seal is broken or missing. Consult a licensed healthcare professional if pregnant, nursing of if symptoms worsen or persist for more than a few days. Keep out of reach of children.

OTC - PREGNANCY OR BREAST FEEDING SECTION

Consult a licensed healthcare professional if pregnant, nursing or if symptoms worsen or persist for more than a few days.

OTC - KEEP OUT OF REACH OF CHILDREN SECTION

Keep out of reach of children